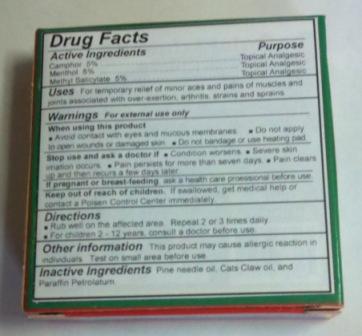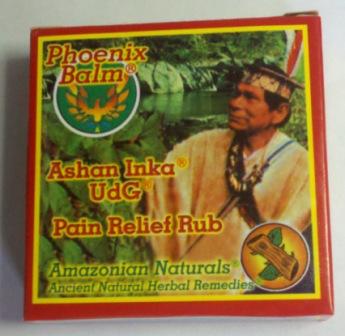 DRUG LABEL: Phoenix Balm
NDC: 24438-001 | Form: OINTMENT
Manufacturer: Amazonian Naturals, Inc.
Category: otc | Type: HUMAN OTC DRUG LABEL
Date: 20111129

ACTIVE INGREDIENTS: CAMPHOR (NATURAL) 50 mg/1 g; MENTHOL 50 mg/1 g; METHYL SALICYLATE 50 mg/1 g
INACTIVE INGREDIENTS: PINE NEEDLE OIL (PINUS SYLVESTRIS); CAT'S CLAW; PETROLATUM

Drug Facts

Active Ingredients

Camphor 5%.................................... Topical Analgesic
Menthol 5% ..................................... Topical Analgesic
Methyl Salicylate 5%........................ Topical Analgesic

Purposes

Topical Analgesic

Uses

For temporary relief of minor aches and pains of muscles and joints associated with over-exertions, arthritis, strains and sprains.

Warnings For external use only.

When using this product

- Avoid contact with eyes and mucous membranes.
- Do not apply to open wounds or damaged skin.
- Do not bandage or use heating pad.

Stop use and ask a doctor if

- Condition Worsens.
- Severe skin irritation occurs.
- Pain persists for more than seven days.
- Pain clears up and then recurs a few days later.

PREGNANCY OR BREAST FEEDING

If pregnant or breast-feeding ask a health care professional before use.

Keep out of reach of children. If swallowed get medical help or contact a Poisen Control Center immediately.

Directions

- Rub well on the affected area. Repeat 2 or 3 times daily.
- For children 2 - 12 years, consult a doctor before use.

Other Information

This product may cause allergic reaction in some people. Test on small area before use.

Inactive Ingredients

Pine needle oil, Cats Claw and Paraffin Petrolatum